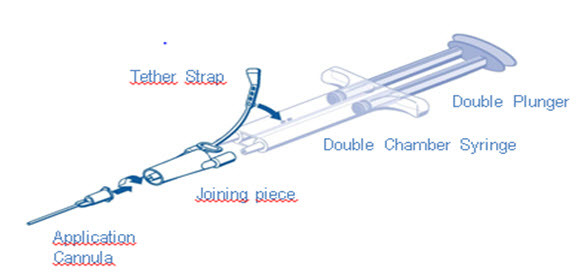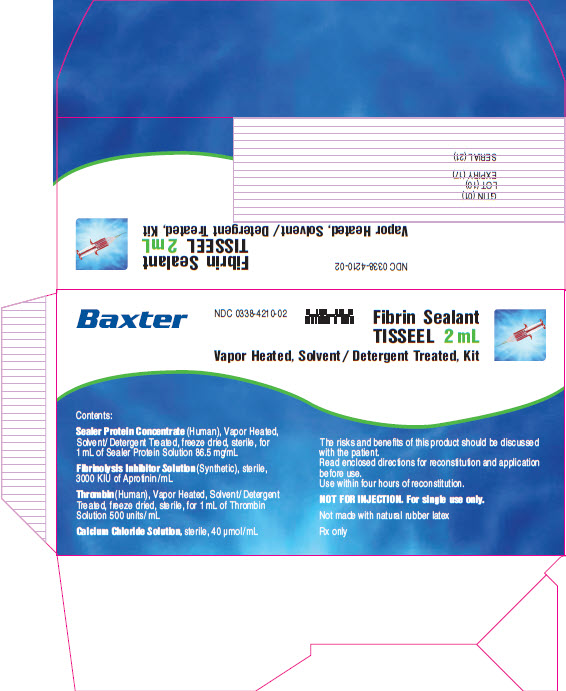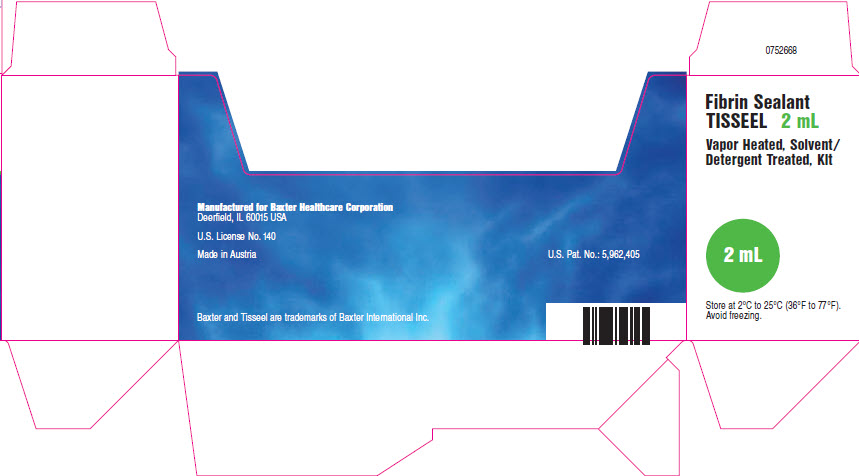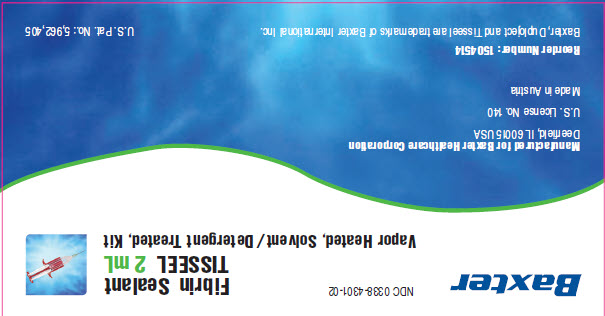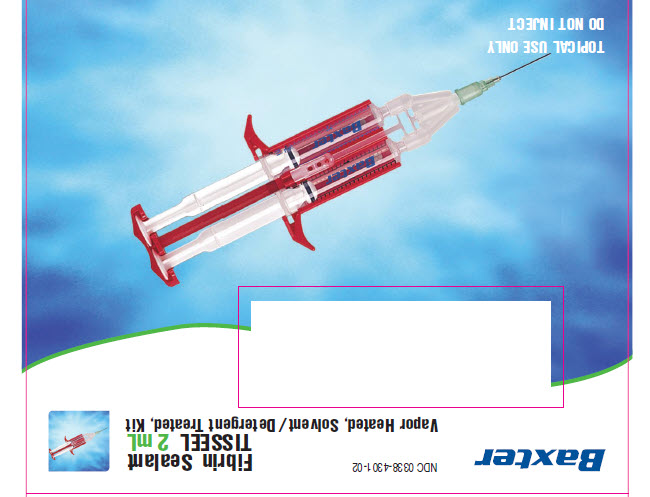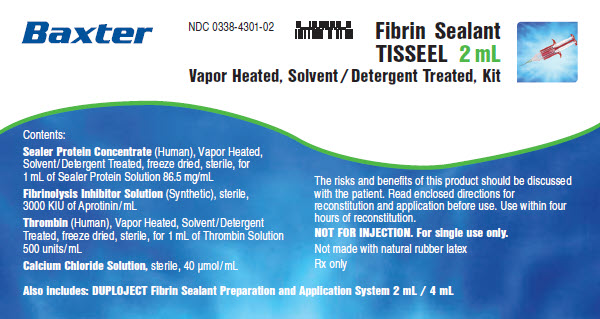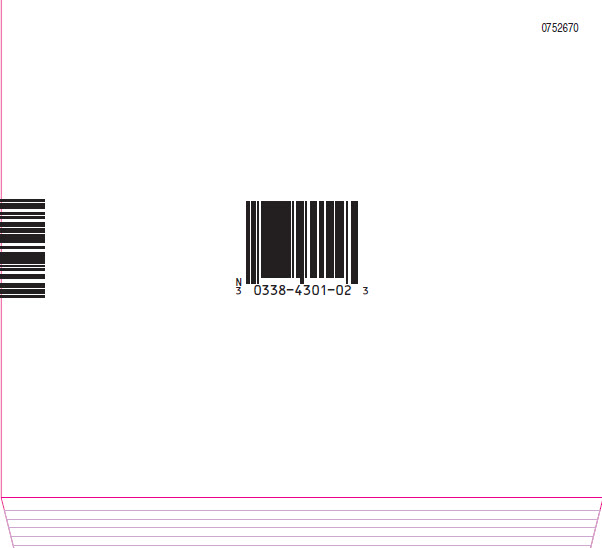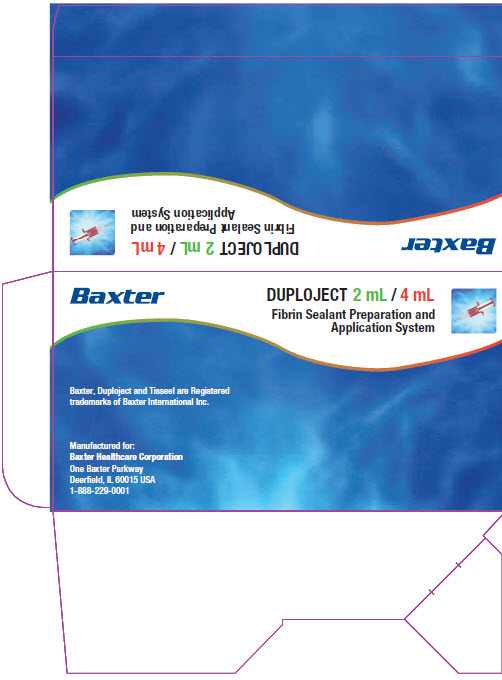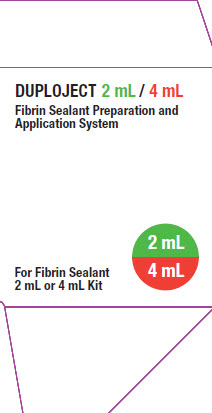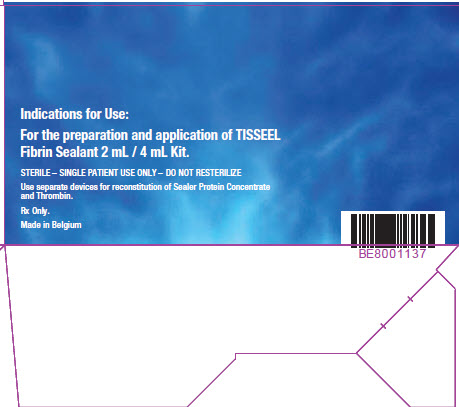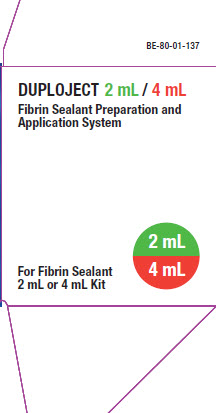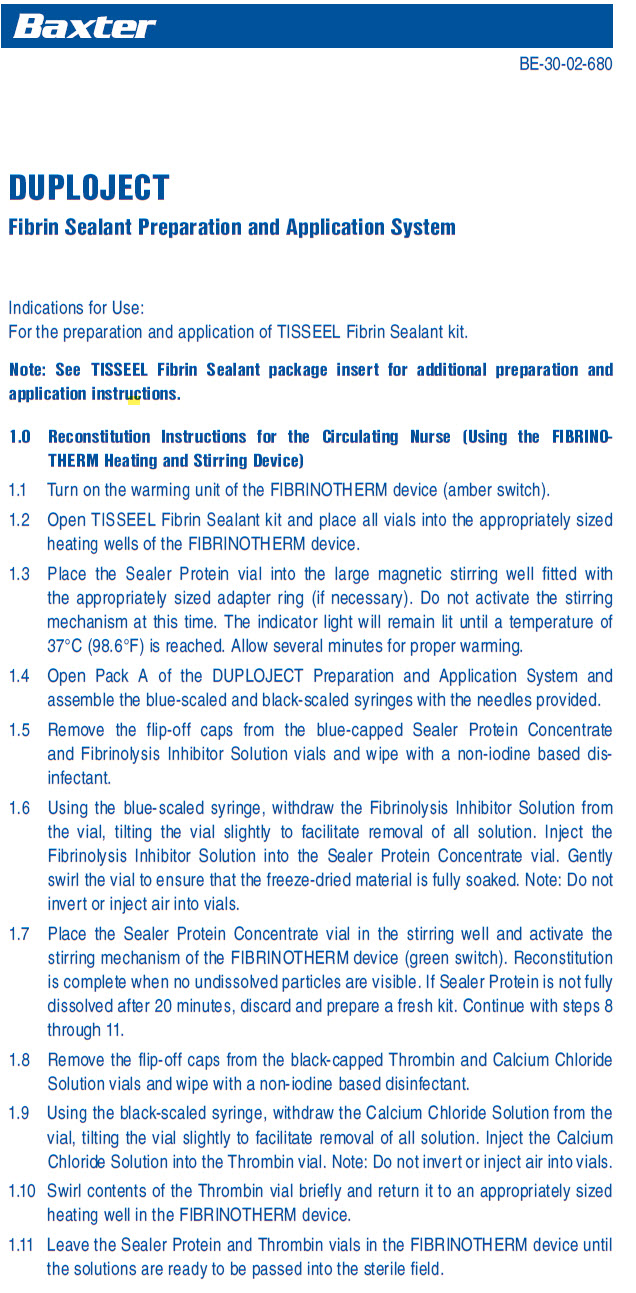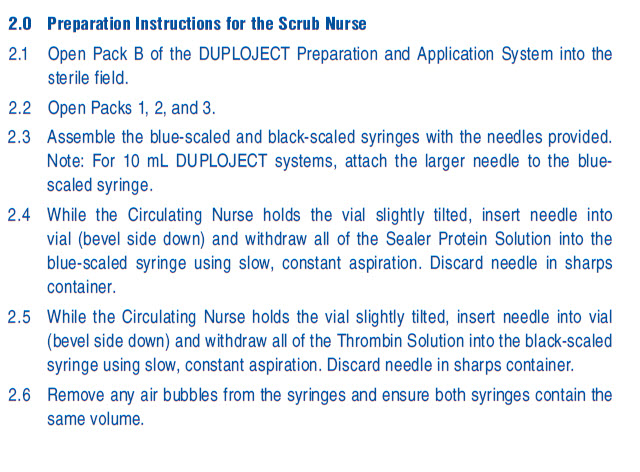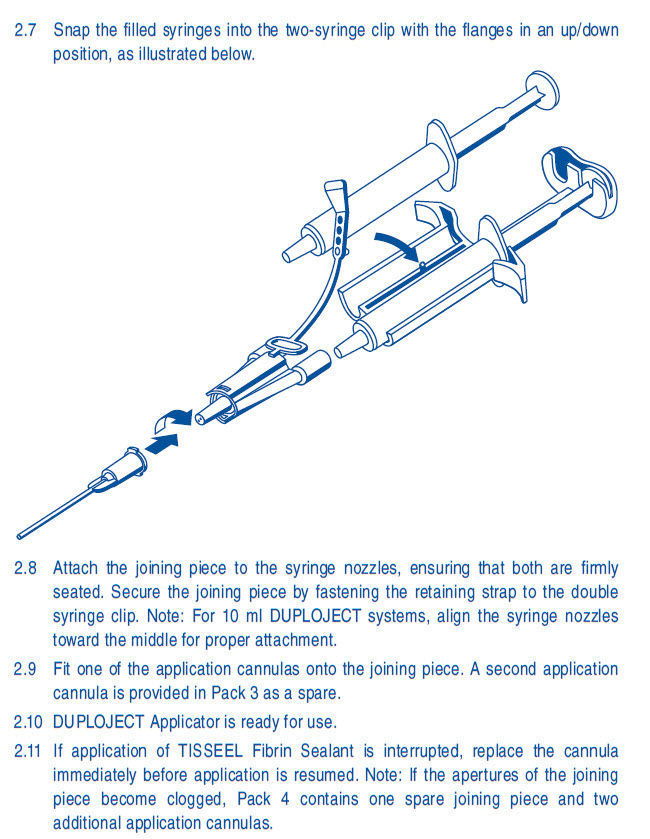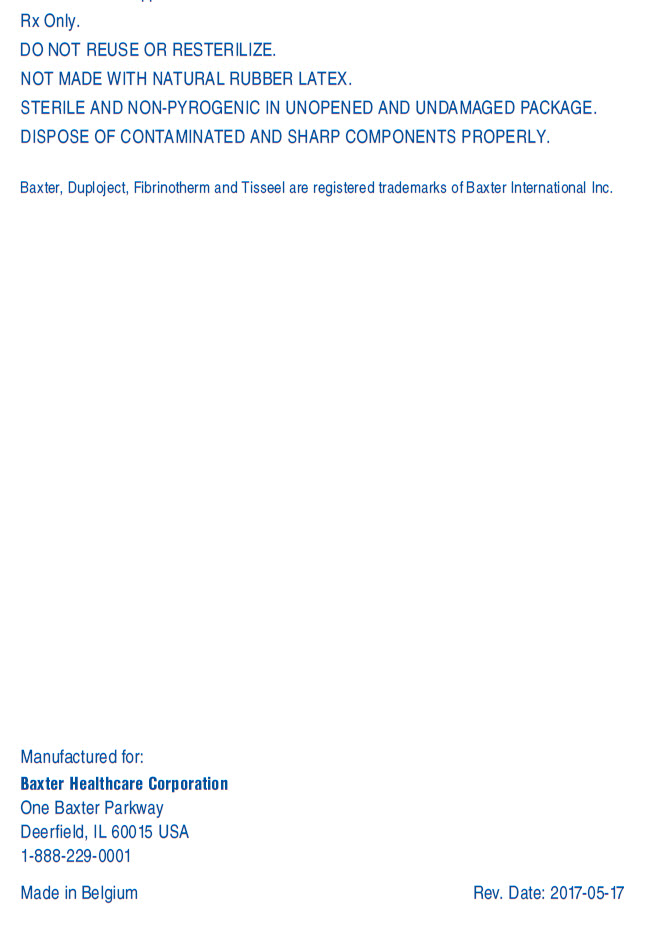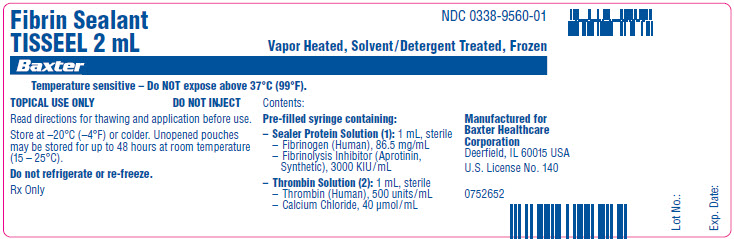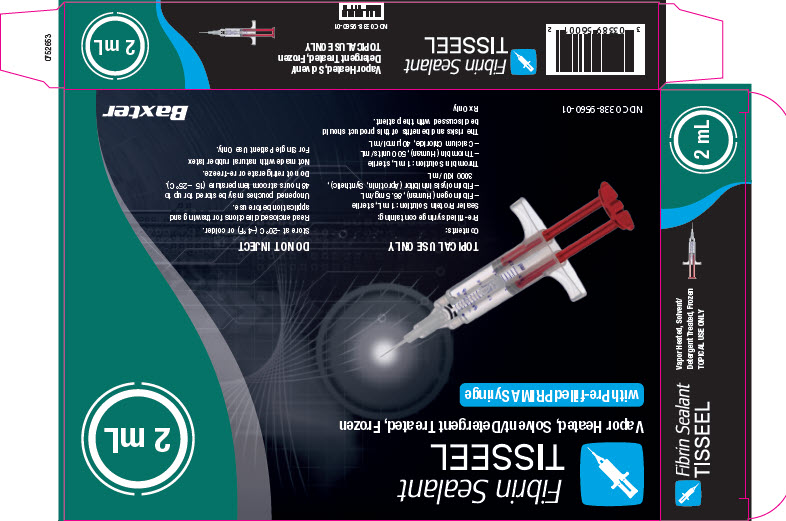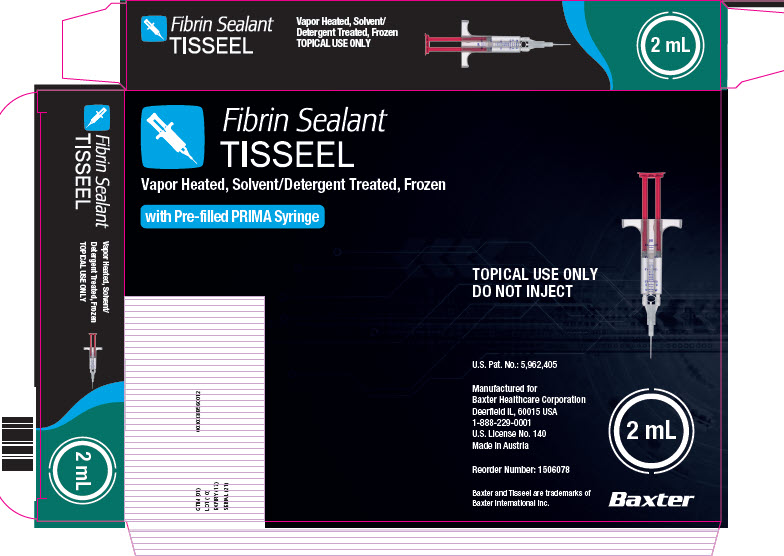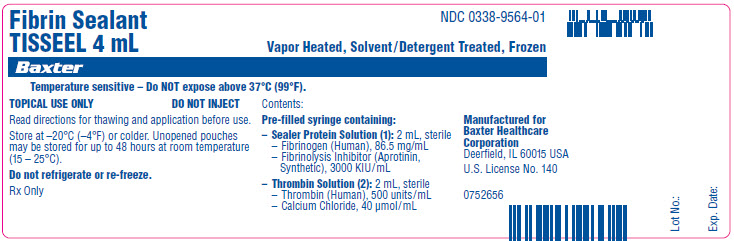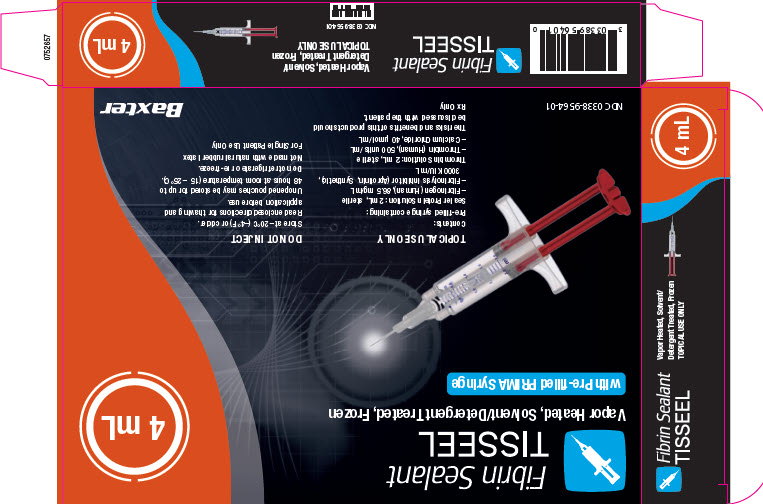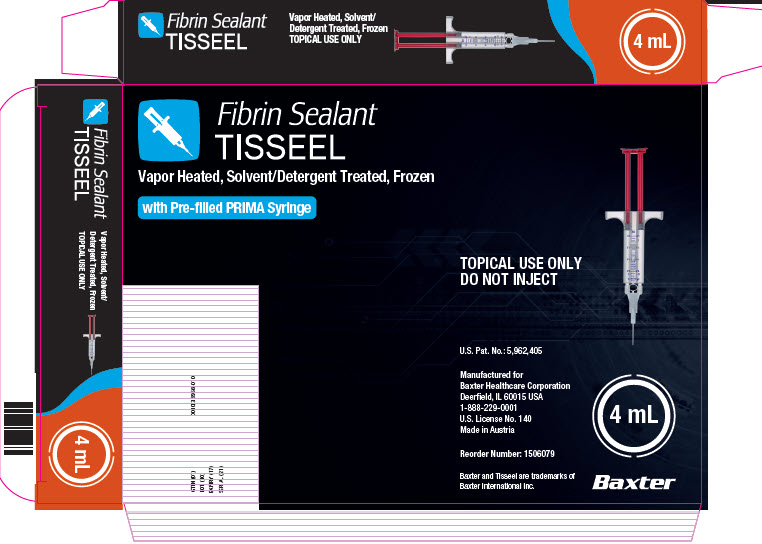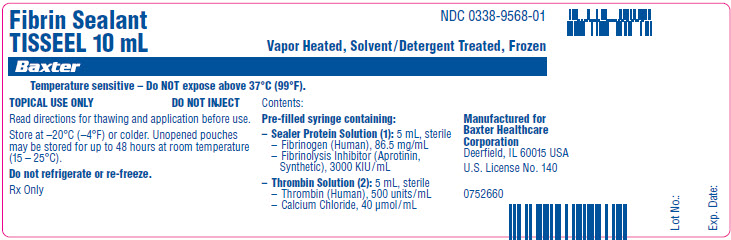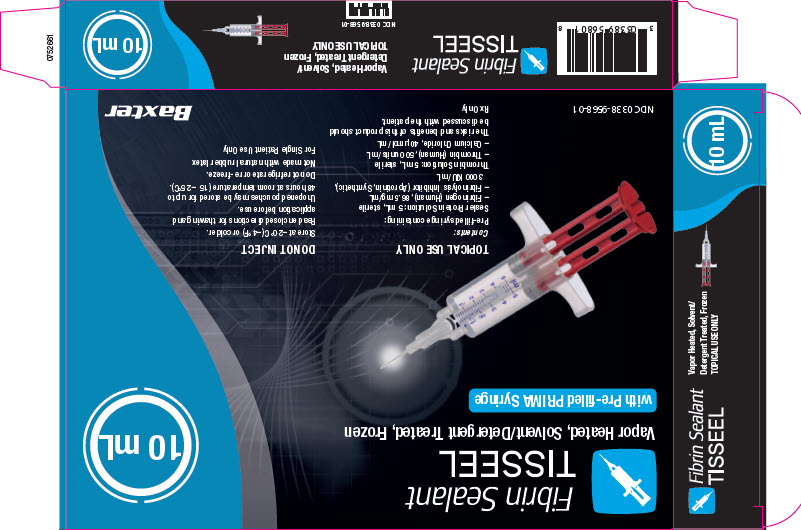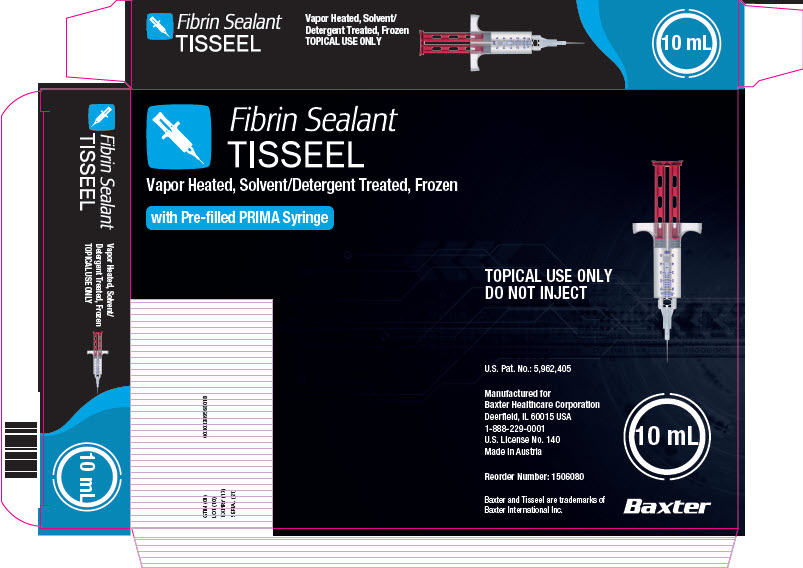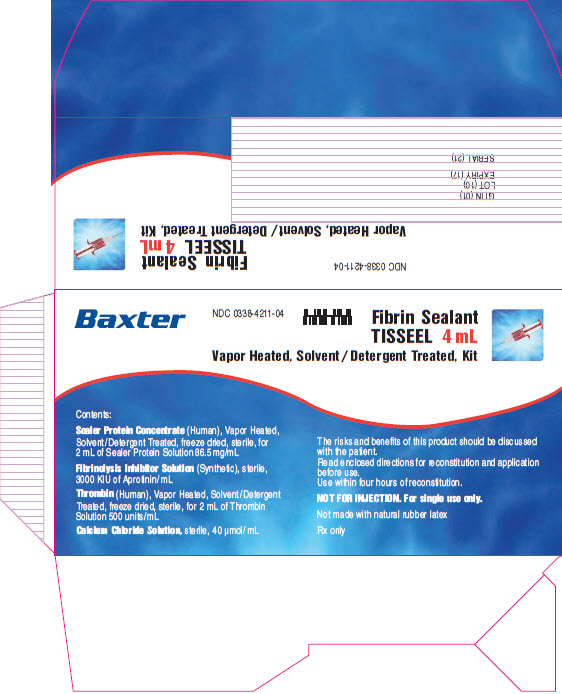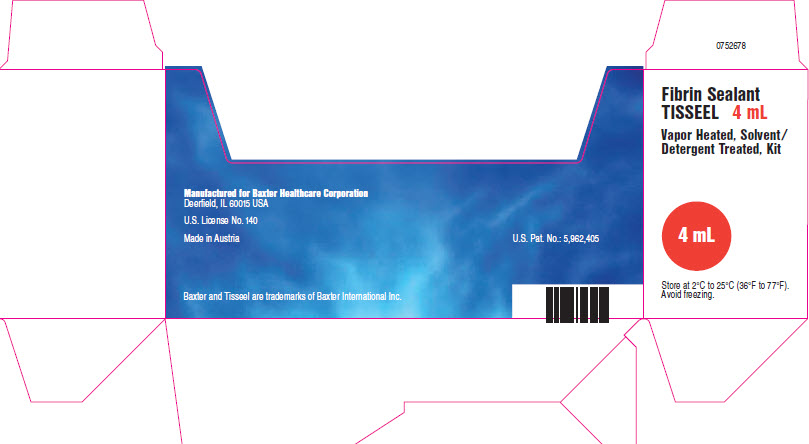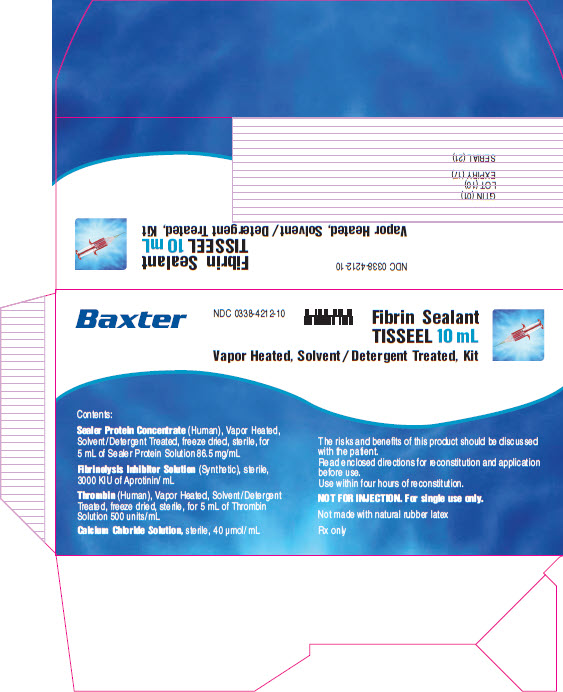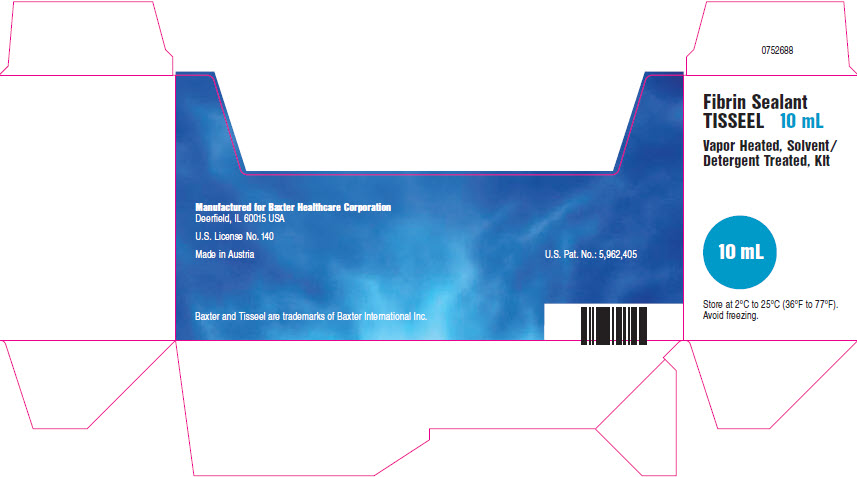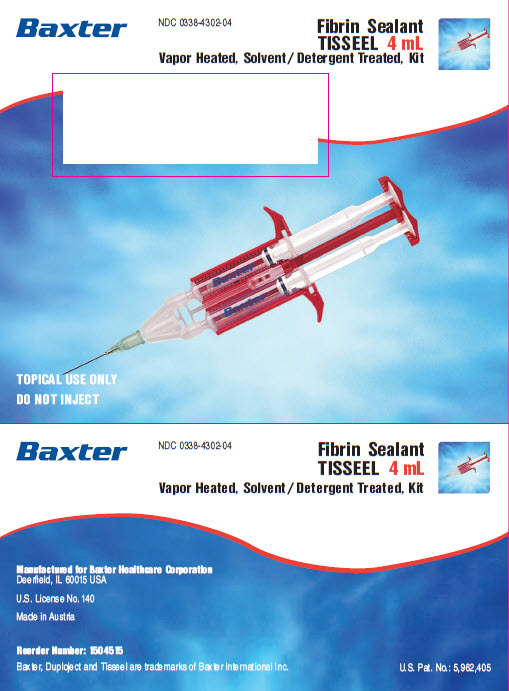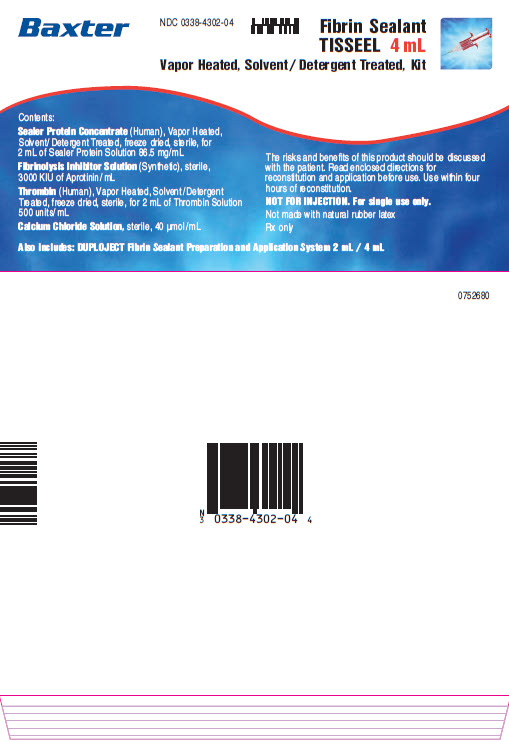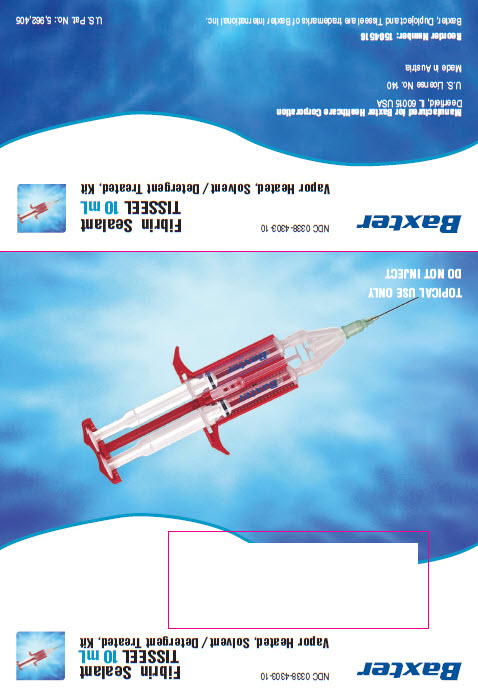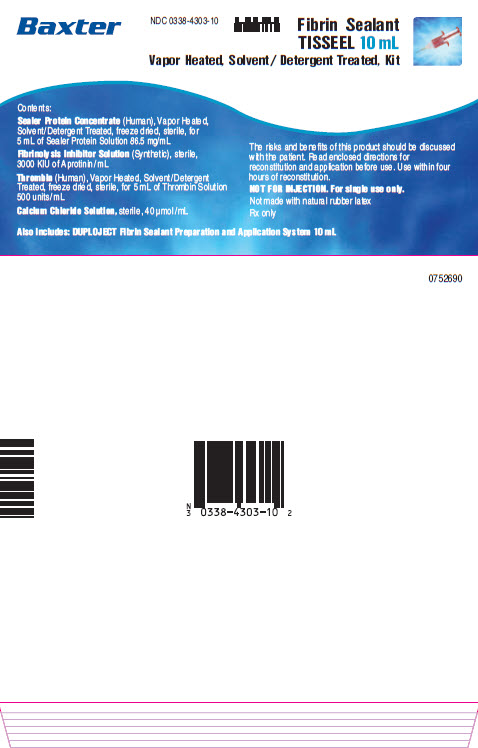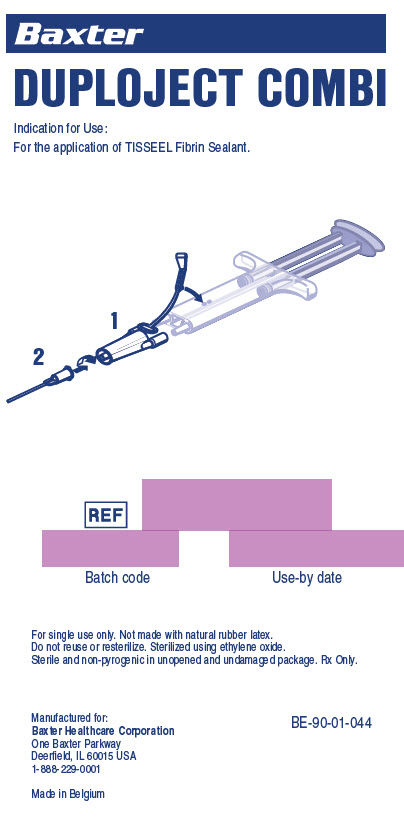 DRUG LABEL: TISSEEL
NDC: 0338-4210 | Form: KIT | Route: TOPICAL
Manufacturer: Baxter Healthcare Corporation
Category: other | Type: PLASMA DERIVATIVE
Date: 20250930

ACTIVE INGREDIENTS: FIBRINOGEN HUMAN 86.5 mg/1 mL; HUMAN THROMBIN 500 [iU]/1 mL
INACTIVE INGREDIENTS: ALBUMIN HUMAN; HISTIDINE; NIACINAMIDE; POLYSORBATE 80; TRISODIUM CITRATE DIHYDRATE; ALBUMIN HUMAN; SODIUM CHLORIDE; APROTININ 3000 [iU]/1 mL; WATER; CALCIUM CHLORIDE 40 umol/1 mL; WATER

HIGHLIGHTS OF PRESCRIBING INFORMATION

These highlights do not include all the information needed to use TISSEEL safely and effectively. See full prescribing information for TISSEEL.
TISSEEL [Fibrin Sealant] Frozen solution and lyophilized powder for solution for topical use only
Initial U.S. Approval: 1998

RECENT MAJOR CHANGES

Indication and Usage (1) 09/2025
Dosage and Administration (2.1, 2.2, 2.3) 09/2025

1 INDICATIONS AND USAGE

Hemostasis: TISSEEL is a fibrin sealant indicated for use as an adjunct to hemostasis in adult and pediatric patients undergoing surgery when control of bleeding by conventional surgical techniques (such as suture, ligature, and cautery) is ineffective or impractical. TISSEEL is effective in heparinized patients. (1)

Sealing: TISSEEL is a fibrin sealant indicated in adult and pediatric patients as an adjunct to standard surgical techniques (such as suture and ligature) to prevent leakage from colonic anastomoses following the reversal of temporary colostomies. (1)

2 DOSAGE AND ADMINISTRATION

For Topical Use Only. (2.1)

- The recommended dosage of TISSEEL is based on the surface area of the wound to be covered to stop bleeding. (2.1)
- Apply TISSEEL as a thin layer by dripping or spraying using cannula or spray set. (2.1, 2.4)
- Ensure that the amount of TISSEEL to be applied is sufficient to entirely cover the intended application area. (2.1)

3 DOSAGE FORMS AND STRENGTHS

TISSEEL Kit (Freeze-Dried) is supplied as 2 mL, 4 mL and 10 mL (total volume) pack sizes with and without the DUPLOJECT Fibrin Sealant Preparation and Application System (3). TISSEEL Pre-filled Syringe (Frozen) is supplied as 2 mL, 4 mL and 10 mL (total volume) pack sizes with DUPLOJECT COMBI. (3)

4 CONTRAINDICATIONS

- Do not inject directly into the circulatory system or into highly vascularized tissue, such as nasal mucosa. (4)
- Do not use in individuals with a known hypersensitivity to aprotinin. (4, 5.1,6.2)
- Do not use for the treatment of severe or brisk arterial or venous bleeding. (4)
- Do not spray where the minimum recommended distance from the applicator tip to the target site cannot be assured. (4)

5 WARNINGS AND PRECAUTIONS

- Hypersensitivity Reactions: TISSEEL contains aprotinin, a protein known to be associated with anaphylactic reactions. (5.1, 6.2)
- Air or Gas Embolism: To reduce the risk of potential life-threatening gas embolism, spray using only the appropriate pressurized gas at the recommended pressure and distance. For Open Surgical procedures, use the EASYSPRAY device connected to CO2, Medical Air or Nitrogen. For Minimally Invasive Surgery procedures use the DUPLOSPRAY MIS device connected only to CO2. (5.2)
- TISSEEL may be denatured when exposed to solutions containing alcohol, iodine or heavy metals. (5.2)
- Use in Surgery: When using TISSEEL in surgery do not inject intravascularly. (4, 5.3, 6.2)
- Neurosurgical Procedures: Safety has not been evaluated in neurosurgical procedures. (5.4)
- Transmission of Infectious Agents: TISSEEL is made from pooled human plasma and may carry a risk of transmitting infectious agents. (5.4)

6 ADVERSE REACTIONS

Most common adverse reaction include hypersensitivity including anaphylactic reaction and anaphylactic shock. (6)

To report SUSPECTED ADVERSE REACTIONS, contact Baxter Healthcare Corporation at 1-888-229-0001 or FDA at 1-800-FDA-1088 or www.fda.gov/medwatch.

7 DRUG INTERACTIONS

Oxidized cellulose-containing preparations can reduce the efficacy of TISSEEL and should not be used as carrier materials. (7)

FULL PRESCRIBING INFORMATION

1 INDICATIONS AND USAGE

Hemostasis: TISSEEL is a fibrin sealant indicated for use as an adjunct to hemostasis in adult and pediatric patients undergoing surgery when control of bleeding by conventional surgical techniques (such as suture, ligature, and cautery) is ineffective or impractical. TISSEEL is effective in heparinized patients.

Sealing: TISSEEL is a fibrin sealant indicated in adult and pediatric patients as an adjunct to standard surgical techniques (such as suture and ligature) to prevent leakage from colonic anastomoses following the reversal of temporary colostomies.

2 DOSAGE AND ADMINISTRATION

2.1 Recommended Dosage

FOR TOPICAL USE ONLY

The recommended dosage of TISSEEL is based on the surface area of the wound to be covered to stop bleeding.
The approximate surface areas covered by each package size of TISSEEL are listed in Table 1:

Table 1: Surface Area Coverage
Required package size of TISSEEL | Maximum coverage using spray | Maximum coverage using cannula
2 mL; 4 mL; 10 mL | 100 cm^2; 200 cm^2; 500 cm^2 | 8 cm^2; 16 cm^2; 40 cm^2

- Ensure that the amount applied is sufficient to entirely cover the intended application area. Avoid application beyond the intended area.
- Allow at least 2 minutes after application to achieve sufficient polymerization.
- If repeat application is needed, dry the site as much as possible before reapplying. Reapply after removing residues from the prior application or before polymerization takes place since TISSEEL may not adhere firmly to a polymerized layer.
- Only a thin layer of TISSEEL should be applied. Excessive thickness of the fibrin layer may interfere with the wound healing process.

2.2 Preparation and Reconstitution of TISSEEL Kit (Freeze-Dried)

The procedures described below are provided as general guidance.

Do not expose to temperatures above 37°C.
Do not microwave.
After reconstitution, the product must be used within 4 hours and must not be refrigerated or frozen.

Use aseptic technique when preparing and reconstituting the fibrin sealant components.
Prior to reconstitution of the fibrin sealant components, clean the rubber stoppers of all vials with a suitable disinfectant, taking care to avoid direct contact with the product.

The Sealer Protein Concentrate is dissolved with the Fibrinolysis Inhibitor Solution (Aprotinin) to form the Sealer Protein Solution. Air-bubbles may make the reconstituted Sealer Protein Solution appear turbid, but such turbidity does not compromise the efficacy or usability of the product. Thrombin Powder is dissolved in the Calcium Chloride Solution to form the Thrombin Solution. Always use separate syringes and cannulas for reconstituting the two solutions to prevent premature clotting. Both solutions should be clear or slightly opalescent. Check the reconstituted solutions visually prior to administration. Do not use solutions which are cloudy, discolored, have deposits, or other changes in their appearance.

1. Reconstitution using the FIBRINOTHERM device
1a. Pre-warming of TISSEEL Lyo (Kit)

Place all four vials from the TISSEEL Kit into the pre-warmed wells of the FIBRINOTHERM device, using the appropriately sized adapter ring(s), and allow the vials to warm for approximately 3 minutes. The FIBRINOTHERM device maintains a constant temperature of 37°C and enables dissolution of the lyophilized Sealer Protein Concentrate by stirring.

1b. Preparation of Sealer Protein Solution (component 1) (FIBRINOTHERM)

- Remove the caps from the Sealer Protein Concentrate and the Fibrinolysis Inhibitor Solution vials.
- Transfer the Fibrinolysis Inhibitor Solution into the vial containing the Sealer Protein Concentrate using one cannula and the blue-scaled syringe provided in the sterile kit for reconstitution.
- Gently swirl the vial to ensure that the product is completely soaked.
- Place the vial into the largest opening of the FIBRINOTHERM device (use an appropriate adaptor, if necessary).
- Switch on the magnetic stirrer and stir until the Sealer Protein Concentrate is dissolved.
- Reconstitution is complete when no particles are visible.
- If particles are present, dissolution can be facilitated by horizontal agitation of the vial (avoid shaking vertically) and keep on stirring the solution at 37°C until the Sealer Protein Concentrate is dissolved completely.
- Turn off the magnetic stirrer when dissolution is complete.

Notes:

- If the Sealer Protein Concentrate has not fully dissolved within 20 minutes discard the vial and prepare a fresh kit.
- Keep the Sealer Protein Solution at 37°C or at room temperature without stirring if it is not used immediately. To ensure homogeneity, briefly swirl the Sealer Protein Solution before drawing it up into the blue-scaled syringe, provided in the sterile kit for application.

1c. Preparation of Thrombin Solution (component 2) (FIBRINOTHERM)

- Remove the caps from the Thrombin Powder and the Calcium Chloride Solution vials.
- Transfer the Calcium Chloride Solution into the Thrombin vial. Use the second cannula and the black-scaled syringe provided in the sterile kit for reconstitution.
- Swirl briefly to dissolve the lyophilized powder and place the vial into the appropriate opening of the FIBRINOTHERM device.
- Keep the Thrombin Solution at 37°C or at room temperature if it is not used immediately. To ensure homogeneity, briefly swirl the Thrombin solution before drawing it up into the black-scaled syringe, provided in the sterile kit for application.

Transferring to the Sterile Field
For transfer of the Sealer Protein and Thrombin Solutions to the sterile field, the circulating nurse should disinfect the tops of the vials with a germicidal solution and allow to dry. The scrub nurse should withdraw the sterile solutions while the circulating nurse holds the non-sterile vials. Slowly withdraw the solution, by firm constant aspiration, to reduce the risk of large air bubbles.

See FIBRINOTHERM device manual for complete operating instructions. If a FIBRINOTHERM device is not available, contact Baxter (1-800-229-0001) for assistance.

2.3 Preparation of TISSEEL Pre-Filled Syringe (Frozen)

Do not expose to temperatures above 37˚C. Do not microwave.
Do not refrigerate or re-freeze after thawing.
Do not use TISSEEL (frozen) until it is completely thawed and warmed to 33 - 37˚C. To facilitate removal of the tip cap from the syringe, rock the tip cap by moving it backward and forward, then pulling the protective cap off the syringe.

Sterile Water Bath: Transfer inner pouch to the sterile field, remove pre-filled syringe from inner pouch and place directly into sterile water bath ensuring the syringe is completely immersed in the water. Maintain the product at 33-37°C until use. Once the package is opened or the product is warmed to 33-37°C, it must be used within 4 hours.

Non-Sterile Water Bath: Maintain the pre-filled syringe in pouches and place into a water bath outside the sterile field ensuring the pouches remain submerged. Remove from the water bath after thawing and warming, dry the external pouch and transfer inner pouch with pre-filled syringe onto the sterile field. Maintain the product at 33-37°C until use. Once the package is opened or the product is warmed to 33-37°C, it must be used within 4 hours.

Incubator: Maintain the pre-filled syringe in pouches and place into an incubator. Remove from the incubator after thawing and warming. Transfer inner pouch with pre-filled syringe onto the sterile field. Maintain the product at 33-37°C until use. Once the package is opened or the product is warmed to 33-37°C, it must be used within 4 hours.

Table 2: Approximate Water Bath or Incubator Thawing and Warming Times
Pack Size | Sterile Water Bath (Pouches Removed) 33 - 37°C | Non-Sterile Water Bath (In Pouches) 33 - 37°C | Incubator (In Pouches) 33 - 37°C
2 mL | 5 minutes | 15 minutes | 40 minutes
4 mL | 5 minutes | 20 minutes | 50 minutes
10 mL | 10 minutes | 35 minutes | 90 minutes

Room Temperature Thawing: Unopened pouches can be stored for up to 48 hours at room temperature (15-25°C). Before use, warm the product to 33-37°C and apply immediately. The total thawing and warming time cannot exceed 48 hours.

Table 3: Approximate Room Temperature Thawing Times
Pack Size | Room Temperature (In Pouches) 15-25°C
2 mL | 80 minutes
4 mL | 90 minutes
10 mL | 160 minutes

Table 4: Approximate Water Bath or Incubator Warming Times for Thawed Product
Pack Size | Sterile Water Bath (Pouches Removed) 33 - 37°C | Non-Sterile Water Bath (In Pouches) 33 - 37°C | Incubator (In Pouches) 33 - 37°C
2 mL | 2 minutes | 5 minutes | 16 minutes
4 mL | 2 minutes | 8 minutes | 21 minutes
10 mL | 4 minutes | 12 minutes | 35 minutes

The Sealer Protein and the Thrombin Solutions should be clear or slightly opalescent. Do not use solutions that are cloudy, discolored, have deposits, or other changes in their appearance. If one of the above occurs, dispose of the solutions.

The thawed Sealer Protein Solution should be liquid but slightly viscous. If the solution has the consistency of a solidified gel, do NOT use TISSEEL.

2.4 Method of Application

TISSEEL Kit (Freeze-Dried)

Apply TISSEEL using the DUPLOJECT Fibrin Sealant Preparation and Application System or an equivalent delivery system (including open and minimally invasive spray devices) cleared by FDA for use with TISSEEL. Specific instructions for the use of TISSEEL in conjunction with each cleared delivery device are provided with the device.

TISSEEL Pre-filled Syringe (Frozen)

Apply pre-filled TISSEEL using the joining piece and application cannula accessory devices provided with the product or an equivalent delivery device (including open and minimally invasive spray devices) cleared by the FDA for use with TISSEEL.

DUPLOJECT COMBI Instructions (see Figure 1)

1. Expel all air from the syringe prior to attaching any application device.
2. Align the joining piece and tether to the side of the syringe with the tether strap hole.
3. Connect the nozzles of the double chamber ready-to-use syringe to the joining piece, ensuring that they are firmly attached.
4. Secure the joining piece by fastening the tether strap to the double chamber ready-to-use syringe.
5. If the tether strap tears, use the spare joining piece provided in the kit. If a spare joining piece is not available, the system can still be used if care is taken to ensure that the connection is secure and leak-proof.
6. Do NOT expel the air remaining inside the joining piece.
7. Attach an application cannula on to the joining piece.
8. Do NOT expel the air remaining inside the joining piece and inside the application cannula until the start of the actual application because this may clog the application cannula.
Note: Interruption of TISSEEL application causes clogging in the cannula. Replace the cannula immediately prior to resuming application. If the opening of the joining piece (Y-connector) facing the cannula is clogged, use the spare joining piece provided in the package.

Figure 1
DUPLOJECT COMBI

TISSEEL must be sprayed only onto application sites that are visible. Dry the site of application as much as possible. The surface area of the wound needs to be dried using standard techniques (e.g. intermittent application of compresses, swabs, use of suction devices). Do not use pressurized air or gas to dry the site.

When applying TISSEEL using a spray device, utilize the recommended gas, pressure and distance from tissue within the ranges recommended by the manufacturer as follows:

Table 5: Recommended Application Equipment, Gas and Parameters
Surgery | Spray set / Applicator tips to use | Pressure regulator to use | Gas | Distance | Spray Pressure
Open surgery | TISSEEL /ARTISS; Spray Set | EASY SPRAY; Pressure Regulator | Medical grade CO2 [Medical grade CO2 is the preferred gas for application, however compressed Air or Nitrogen are acceptable gasses for administration of TISSEEL in open surgery.] , Compressed; Air or Nitrogen | 10-15 cm | 1.5-2.0 bar; (21.8-29.0 psi)
Laparoscopic/ minimally invasive procedures | DUPLOSPRAY MIS Applicator 20 cm; DUPLOSPRAY MIS Applicator 30 cm; DUPLOSPRAY MIS Applicator 40 cm; 360º Flexible; Applicator 40 cm; Replaceable tip | DUPLOSPRAY; MIS Regulator | CO2 Only | Range 2-5 cm; 3 cm recommended | 1.18-1.50 bar; (17-22 psi)

Apply TISSEEL as a thin layer by dripping or spraying using a cannula or spray set approved for use with TISSEEL. To reduce the risk of potentially life-threatening gas embolism, spray TISSEEL using only the appropriate pressurized gas within the pressure range and distance recommended in the device Instructions For Use (see Warnings and Precautions (5.2)).

In cases where very small volumes (1-2 drops) are required, expel and discard the first several drops from the application cannula immediately before application to ensure administration of adequately mixed TISSEEL.

Vials and pre-filled syringes are for single-patient use only. Discard any unused product.

It is strongly recommended that every time TISSEEL is applied to a patient, the name and batch number of the product are recorded in order to maintain a link between the patient and the batch of the product.

3 DOSAGE FORMS AND STRENGTHS

TISSEEL Kit (Freeze-Dried) is supplied as 2 mL, 4 mL and 10 mL (total volume) pack sizes with and without the DUPLOJECT Fibrin Sealant Preparation and Application System. TISSEEL Pre-Filled Syringe (Frozen) is supplied as 2 mL, 4 mL and 10 mL (total volume) pack sizes with the DUPLOJECT COMBI.

4 CONTRAINDICATIONS

TISSEEL is contraindicated for the following.
2. Intravascular Application: Do not inject TISSEEL directly into the circulatory system or into highly vascularized tissue, such as nasal mucosa. Intravascular application of TISSEEL can lead to intravascular coagulation, can result in life-threatening thromboembolic events (see Warnings and Precautions (5.3) and Adverse Reactions (6.2)). TISSEEL must be applied with caution to minimize any risk of intravascular application, for example in coronary bypass surgery.
3. Aprotinin Hypersensitivity: Do not use TISSEEL in individuals with a known hypersensitivity to aprotinin (see Warnings and Precautions (5.1) and Adverse Reactions (6)).
4. Severe or Brisk Bleeding: Do not use TISSEEL for treatment of severe or brisk arterial or venous bleeding. In these situations, TISSEEL will be washed away in the flow of blood before hemostasis can be attained.
5. Application below minimum recommended distance from target site: Do not spray TISSEEL where the minimum recommended distance from the applicator tip to the target site cannot be assured.

5 WARNINGS AND PRECAUTIONS

5.1 Hypersensitivity Reactions

Hypersensitivity reactions including life-threatening anaphylactic reactions have occurred with the use of TISSEEL [see Adverse Reactions (6.2)]. Aprotinin included in TISSEEL for its antifibrinolytic properties is associated with hypersensitivity including anaphylactic reactions. Patients who receive repeated applications of TISSEEL over time or in the same setting, or who previously received systemic aprotinin are at a higher risk for hypersensitivity reactions. Hypersensitivity reactions may occur with initial or subsequent applications of TISSEEL.

Document the use of TISSEEL in the patient's records, noting that TISSEEL contains aprotinin, as required for all aprotinin-containing products. Monitor patients for signs and symptoms of hypersensitivity reactions which include bradycardia, tachycardia, hypotension, flushing, bronchospasm, wheezing, dyspnea, nausea, urticaria, angioedema, pruritus, erythema and paresthesia. Discontinue administration of TISSEEL in the event of hypersensitivity reactions and manage according to clinical practice. Remove remaining product from the application site.

5.2 Air or Gas Embolism

Life threatening or fatal air or gas embolism, tissue rupture or gas entrapment with compression, have occurred when Fibrin Sealants were administered using pressurized gas with open regulator spray devices [see Adverse Reactions (6)]. This can occur if a spray device is used at higher than recommended pressures and in closer than recommended proximity to the tissue surface. The solubility of compressed CO2 is greater than either compressed N2 or Air thereby reducing the potential effect of embolization.

Regardless of the type of gas used, to reduce the incidence of embolization, spray TISSEEL using only the recommended regulator, set within the recommended pressure range, with the appropriate applicator positioned at the recommended distance in Table 5.

Monitor changes in blood pressure, pulse, oxygen saturation and end tidal CO2 due to the possibility of air or gas embolism.

Use only spray catheters or applicators approved for use with TISSEEL.

Do not spray TISSEEL in enclosed body areas using the EASYSPRAY device. Spray only on the visible application sites.

For Open Surgical Procedures, use the EASYSPRAY Pressure Regulator connected to medical grade CO2, compressed Air or a Nitrogen compressed gas source along with the TISSEEL/ARTISS spray set (see Method of Application (2.4)).

For Minimally Invasive Surgery Proceduresin enclosed body areas use of the DUPLOSPRAY MIS device connected only to compressed CO2, along with DUPLOSPRAY applicator is recommended. The DUPLOSPRAY MIS device is specifically designed to prevent over pressurization of the body cavity through a dedicated ventline to reduce the risk of gas embolization, (see Method of Application (2.4)).

The Sealer Protein and Thrombin solutions may be denatured by alcohol, iodine or heavy metal ions. If any of these substances have been used to clean the wound area, the area must be thoroughly rinsed before the application of TISSEEL.

5.3 Use in Surgery

When using TISSEEL in surgery, do not inject intravascularly (see Contraindications (4) and Adverse Reactions (6.2)).

5.4 Use in Neurosurgical Procedures

The safety and effectiveness of TISSEEL used alone or in combination with biocompatible carriers in neurosurgical procedures or other surgeries involving confined spaces have not been evaluated, and its use in this setting is not approved by FDA (see Adverse Reactions (6.2) and Drug Interactions (7)).

5.5 Transmission of Infectious Agents

TISSEEL is made from human blood, therefore it may carry a risk of transmitting infectious agents, e.g., viruses, the variant Creutzfeldt-Jakob disease (vCJD) agent and, theoretically the Creutzfeldt-Jakob disease (CJD) agent. All infections thought possibly to have been transmitted by this product should be reported by the physician or other healthcare provider to Baxter Healthcare Corporation at 1-888-229-0001.

6 ADVERSE REACTIONS

6.1 Clinical Trials Experience

Because clinical trials are conducted under widely varying conditions, adverse reaction rates observed in the clinical trials of a drug cannot be directly compared to rates in the clinical trials of another drug and may not reflect the rates observed in practice.

The safety data described in this section reflects exposure of TISSEEL in five clinical trials, Study 1, Study 2, Study 3, Study 4, and Study 5. A total of 452 patients received TISSEEL as an adjunct to hemostasis undergoing surgery when control of bleeding by conventional surgical techniques is ineffective or impractical in Study 1, Study 2, Study 3, and Study 4, or for sealing as an adjunct to standard surgical technique to prevent leakage from colonic anastomoses following the reversal of temporary colostomies in Study 5. The mean volume of TISSEEL applied was 5.3 mL (range 0.2 – 20.0 mL). The follow up duration for Study 1 was 30 days. The follow up duration for Study 2 and Study 3 was 6 months. The follow up duration for Study 4 was a maximum of 167 days. The follow up duration for Study 5 was a maximum of 69 days (see Clinical Studies (14)).

Increased D-Dimer levels have been observed during a clinical study in cardiovascular surgery (see Clinical Studies (14)), but did not exceed values reported in the literature occurring after this type of surgery. Postoperatively increased D-Dimers can result at least partly from the degradation of Fibrin Sealant.

There were no reports of serious, associated adverse reactions reported above 1% in clinical studies.

6.2 Post-Marketing Experience

Because adverse reactions are reported voluntarily and the population is of uncertain size, it is not always possible to reliably estimate the frequency of these reactions.

The following adverse reactions have been reported in the post-marketing experience.

Immune System Disorders: Hypersensitivity, including anaphylactic reaction and anaphylactic shock. Anaphylactic reactions and anaphylactic shock have included fatal outcomes.
Vascular Disorders: Hypotension, flushing, embolism, including cerebral artery embolism, cerebral infarction*, air embolism**
Skin and subcutaneous Tissue Disorders: Angioedema, erythema, impaired healing, pruritus, urticaria
Cardiac Disorders: Bradycardia, tachycardia
Respiratory Disorders: Bronchospasm, dyspnea, wheezing
Gastrointestinal Disorders: Nausea
Nervous System Disorders: Paresthesia
* As a result of intravascular application into the superior petrosal sinus
** As with other fibrin sealants life-threatening/fatal air or gas embolism when using devices with pressurized air or gas occurred; this event appears to be related to an inappropriate use of the spray device (e.g. at higher than recommended pressure and in close proximity to the tissue surface),

Class effect: Manifestations of hypersensitivity or allergic reactions associated with the class of fibrin sealant/hemostatic products include: application site irritation, chest discomfort, chills, headache, lethargy, restlessness and vomiting.

There have been reports of serious adverse events such as paralysis and other compressive complications possibly related to the use of fibrin sealants in combination with resorbable hemostatic agents. There have also been reports of fatalities following the misadministration of topical thrombin (see Warnings and Precautions (5.4)).

7 DRUG INTERACTIONS

Oxidized cellulose-containing preparations can reduce the efficacy of TISSEEL and should not be used as carrier materials. No interaction studies have been performed.

8 USE IN SPECIFIC POPULATIONS

8.1 Pregnancy

Risk Summary

There are no direct or controlled studies of TISSEEL in pregnant women. No animal reproductive and developmental toxicity studies have been conducted with TISSEEL. It is also not known whether TISSEEL can cause fetal harm when administered to a pregnant woman or can affect reproduction capacity. Some viruses, such as parvovirus B19, are particularly difficult to remove or inactivate. Parvovirus B19 most seriously affects pregnant women (fetal infection). In the United States general population, the estimated background risk of major birth defects and miscarriage in clinically recognized pregnancies is 2% to 4% and 15% to 20%, respectively.

8.2 Lactation

Risk Summary

There is no information regarding the presence of TISSEEL in human milk, the effects on the breastfed infant, or the effects on milk production. The developmental and health benefits of breastfeeding should be considered along with the mother’s clinical need for TISSEEL and any potential adverse effects on the breastfed infant from TISSEEL or from underlying maternal condition.

8.4 Pediatric Use

The safety and efficacy of TISSEEL have been established in pediatric patients. The use of TISSEEL as an adjunct to hemostasis was supported by evidence from one clinical study which included 27 pediatric patients aged 1 month to 16 years. The use of TISSEEL as an adjunct to sealing was supported by extrapolation of the data from one clinical study in adult patients [see Adverse Reactions (6) and Clinical Studies (14)].

8.5 Geriatric Use

Clinical studies included 218 patients aged 65 years of age or older treated with TISSEEL (159 undergoing cardiac surgery and 59 undergoing vascular surgery) (see Clinical Studies (14)). No overall differences in safety or effectiveness were observed between these patients and younger patients.

11 DESCRIPTION

TISSEEL [Fibrin Sealant] is a two-component fibrin sealant made from pooled human plasma. When combined, the two components, Sealer Protein and Thrombin mimic the final stage of the blood coagulation cascade.

Sealer Protein (Human)
Sealer Protein (Human) is a sterile, non-pyrogenic, vapor heated and solvent/detergent treated preparation made from pooled human plasma. Sealer Protein (Human) is provided either as a freeze-dried powder for reconstitution with Aprotinin (Synthetic) solution or as a finished frozen solution pre-filled into one side of a dual-chambered syringe. The active ingredient in Sealer Protein (Human) is fibrinogen. Sealer Protein (Human) Solution contains fibrinolysis inhibitor, synthetic Aprotinin, that delays fibrinolysis. Aprotinin (Synthetic) is manufactured by solid phase synthesis from materials completely of non-human/non-animal origin.

Thrombin (Human)
Thrombin (Human) is a sterile, non-pyrogenic, vapor-heated and solvent/detergent treated preparation made from pooled human plasma. Thrombin (Human) is also provided either as a freeze-dried powder for reconstitution with Calcium Chloride Solution or as a finished frozen solution pre-filled into one side of a dual-chambered syringe.

The reconstituted solution or pre-filled syringe contains:
  Sealer Protein Solution
Total protein: 96 – 125 mg/mL
  Fibrinogen: 67 – 106 mg/mL
  Aprotinin (Synthetic): 2250 – 3750 KIU/mL
  Other ingredients include: human albumin, tri-sodium citrate, histidine, niacinamide, polysorbate 80 and water for injection.
Thrombin Solution
Thrombin (Human): 400 – 625 units/mL*
  Calcium Chloride: 36 – 44 µmol/mL
  Other ingredients include: human albumin, sodium chloride and water for injection.
* The potency expressed in units is determined with a clotting assay using an in-house internal standard that has been calibrated against the World Health Organization (WHO) Second International Standard for Thrombin, 01/580. Therefore, a unit (U) is equivalent to an International Unit (IU).

Viral Clearance
TISSEEL is made from pooled human plasma collected at US licensed collection centers. The vapor heat and solvent/detergent treatment steps used in the manufacturing process have been shown to be capable of significant viral reduction. No procedure, however, has been shown to be completely effective in removing viral infectivity from derivatives of human plasma (see Warnings and Precautions (5.4)). Validation studies were conducted using samples drawn from manufacturing intermediates for each of the two human plasma derived components. These samples were spiked with stock virus suspensions of known titers followed by further processing under conditions representative of respective manufacturing steps.

The virus reduction factors (expressed as log10) of manufacturing steps for each of the viruses tested are shown in Table 6.

Table 6: Mean Reduction Factors [log10] for Virus Removal and/or Inactivation
Sealer Protein Component
Manufacturing Step | HIV-1^1 | BVDV^1 | PRV^1 | HAV^2 | MMV^2
Early Manufacturing Steps | n.d. | n.d. | n.d. | n.d. | 2.7
Solvent/Detergent Treatment | ≥4.7 | ≥5.3 | ≥5.5 | n.d. | n.d.
Vapor Heat Treatment | >5.9 | >6.5 | >6.8 | >6.2 | 1.4
Overall Reduction Factor (ORF) | >10.6 | >11.8 | ≥12.3 | >6.2 | 4.1
Thrombin Component
Manufacturing Step | HIV-1^1 | BVDV^1 | PRV^1 | HAV^2 | MMV^2
Thrombin Precursor Mass Capture | 3.2 | 1.8 | 2.5 | 1.5 | 1.2
Vapor Heat Treatment | >5.3 | >5.9 | >6.8 | >4.6 | 1.0
Solvent/Detergent Treatment | ≥5.3 | ≥5.3 | ≥6.2 | n.d. | n.d.
Ion Exchange Chromatography | n.d. | n.d. | n.d. | n.d. | 3.6
Overall Reduction Factor (ORF) | >13.8 | >13.0 | >15.5 | >6.1 | 5.8

^1 Enveloped
  ^2 Non-enveloped
  n.d. = not determined
HIV-1: Human Immunodeficiency Virus 1; HAV: Hepatitis A Virus; BVDV: Bovine Viral Diarrhea Virus, a model for Hepatitis C Virus; PRV: Pseudorabies Virus, a model for lipid enveloped DNA viruses, among those is Hepatitis B Virus; MMV: Mouse Minute Virus, a model for B19V.

In addition, Human Parvovirus B19 (B19V) was used to investigate the upstream Thrombin precursor mass capture step, the Sealer Protein early manufacturing steps and the Thrombin and Sealer Protein vapor heating steps. Using quantitative PCR assays, the estimated B19V log reduction factors were: (a) 1.7 for the Thrombin precursor mass capture step, (b) 3.4 for Sealer Protein early manufacturing steps, (c) >4 for Thrombin vapor heat treatment and (d) 1.0 for Sealer Protein vapor heat treatment.

12 CLINICAL PHARMACOLOGY

12.1 Mechanism of Action

Upon mixing Sealer Protein (Human) and Thrombin (Human), soluble fibrinogen is transformed into fibrin, forming a rubber-like mass that adheres to the wound surface and achieves hemostasis and sealing or gluing of tissues. TISSEEL mimics the final coagulation cascade step as it has all relevant components to form a clot. TISSEEL is effective in heparinized patients and in patients medicated with anti-platelet drugs.

12.2 Pharmacodynamics

Thrombin is a highly specific protease that transforms the fibrinogen contained in Sealer Protein (Human) into fibrin. Fibrinolysis inhibitor, Aprotinin (Synthetic), is a polyvalent protease inhibitor that prevents premature degradation of fibrin. Preclinical studies with different fibrin sealant preparations simulating the fibrinolytic activity generated by extracorporeal circulation in patients during cardiovascular surgery have shown that incorporation of aprotinin in the product formulation increases resistance of the fibrin sealant clot to degradation in a fibrinolytic environment.

12.3 Pharmacokinetics

Unincorporated Aprotinin and its metabolites have a half-life of 30 to 60 minutes and are eliminated by the kidney. Pharmacokinetic studies were not conducted. TISSEEL is expected to be completely resorbed in 10 to14 days.

Because TISSEEL is applied only topically, systemic exposure or distribution to other organs or tissues is not expected.

13 NONCLINICAL TOXICOLOGY

13.1 Carcinogenesis, Mutagenesis, Impairment of Fertility

Long-term animal studies to evaluate the carcinogenic potential of TISSEEL or studies to determine the effect of TISSEEL on fertility have not been performed.

14 CLINICAL STUDIES

The efficacy of TISSEEL was evaluated in five clinical studies, Study 1 (NCT00892957), Study 2 (NCT00161733), Study 3, Study 4, and Study 5 as described below.

Study 1 (Vascular Surgery)
TISSEEL was evaluated in a prospective, controlled, randomized, single-blind, multicenter clinical study against manual compression with gauze pads in 140 patients 33 to 90 year of age undergoing vascular surgery with expanded polytetrafluoroethylene (ePFTE) graft placement (arterio-arterial bypasses and AV shunts for dialysis access in the upper and lower extremity). Patients received standardized dosages of heparin. Protamine was administered after the primary endpoint had been assessed. Long-term antiplatelet treatments were continued perioperatively at the surgeon’s discretion.

Patients were randomly assigned to TISSEEL or control when persistent bleeding at the study suture line was present after surgical hemostasis, i.e., sutures. Eligible bleedings before clamping and treatment application were defined as a minimum of 25% of the suture line bleeds or at least 5 suture line bleedings or any pulsatile or spurting needle hole bleeding. The primary efficacy endpoint was hemostasis achieved at the study suture line at 4 minutes and maintained until surgical closure.

The efficacy results are summarized in Table 7 below.

Table 7: Efficacy Results for Study 1 (Vascular Surgery)
Endpoint | TISSEEL n = 70 | Manual Compression n = 70 | p-value [likelihood ratio chi-square test; 2.5% one sided]
Hemostasis at the study suture line within 4 minutes and maintained until surgical closure | 44 (63%) | 22 (31%) | <0.0001

Study 2 (Cardiac Surgery)
TISSEEL was evaluated in a prospective, parallel design, randomized (1:1), double-blind, multicenter clinical study against an earlier formulation of the product, TISSEEL VH, in 317 patients 19 to 94 years of age undergoing cardiac surgery requiring cardiopulmonary bypass (CPB) and median sternotomy. Patients were treated with TISSEEL or the control product only when hemostasis was not achieved by conventional surgical methods. For the endpoint, hemostasis achieved at the primary treatment site within 5 minutes of treatment and maintained until closure of the surgical wound, TISSEEL was non-inferior to the earlier formulation of the product using a one-sided 97.5% confidence interval on the difference in the proportion of patients successfully treated.

Table 8: Efficacy Result for Study 2 (Cardiac Surgery)
Endpoint | TISSEEL n = 144 | TISSEEL VH n = 144 | One-Sided Confidence Interval
Hemostasis within 5 minutes and maintained until surgical closure | 127 (88%) | 129 (90%) | 97.5%

Study 3 (Cardiac Reoperations)
An earlier formulation of TISSEEL was evaluated in an open-label crossover study against control topical hemostatic agents in 489 patients <10 to 80 years of age undergoing cardiovascular reoperation or resternotomy at 11 institutions. Patients were randomized to TISSEEL or control hemostatic agents when a topical hemostatic was needed at the conclusion of surgery and after all attempts at surgical hemostasis. Patients were crossed to the alternative therapy if bleeding continued after the 5 minute endpoint. At 10 centers, TISSEEL was used after administration of protamine sulfate. At one site, TISSEEL could be used before administration of protamine sulfate. 365 of the 489 patients developed bleeding episodes requiring treatment. For the endpoint (successful hemostasis at 5 minutes), TISSEEL was statistically significantly superior to control topical hemostatic agents in these patients. Similarly, absolute time to cessation of bleeding was statistically significantly shorter for TISSEEL than for control topical hemostatic agents (p<0.0001, Gehan- Wilcoxon test, two sided).

Table 9: Efficacy Result for Study 3 (Cardiac Reoperations)
Endpoint | TISSEEL n = 193 | Control Topical Hemostatic Agent n = 172 | p-value [Pearson c^2 two sided; p <0.0001; intent-to-treat analysis]
Hemostasis within 5 minutes | 159 (82%) | 76 (45%) | <0.0001

1. Pearson c^2 two sided; p <0.0001; intent-to-treat analysis

Study 4 (Splenectomy)
In a single center, open label trial, an earlier formulation of TISSEEL was compared to historical controls in patients undergoing laparotomy for blunt or penetrating traumatic injury to the spleen and/or liver. Use of TISSEEL resulted in the need for statistically significantly fewer splenectomies than control hemostatic maneuvers. TISSEEL did not result in significantly reduced mortality in patients with blunt or penetrating trauma to the liver alone or to the liver and spleen (p=0.067, c^2, one sided).

The population demographics include: 15 – 72 years.

Table 10: Efficacy Result for Study 4 (Splenectomy)
Injury to: | TISSEEL | Historic Controls | p-value*
Spleen | 0/19 | 14/22 | p <0.001
Spleen and Liver | 1/26 | 19/34 | p <0.001

Study 5 (Colostomy Closure)
In a single center, prospective open label study of 118 patients 18 to 73 year of age randomized to standard of care (58 patients) or standard of care plus fibrin sealant (60 patients) for elective colostomy closure after temporary colostomy placement for treatment of traumatic injury to the colon, the earlier version of TISSEEL plus standard of care was also shown to be significantly superior to standard of care alone (p=0.0406, Jonckheere-Terpstra test for ordinal data, two sided) with regard to anastomotic complications (leakage, intra-abdominal abscess formation, re-operation, septic shock, and death).

16 HOW SUPPLIED/STORAGE AND HANDLING

How Supplied

TISSEEL is supplied in the following pack sizes and presentations:

Table 11: NDC Numbers
Pack Size | TISSEEL Kit (Freeze-Dried) | TISSEEL Kit (Freeze-Dried); with DUPLOJECT System | TISSEEL Pre-Filled Syringe (Frozen) with DUPLOJECT COMBI
2 mL | 0338-4210-02 | 0338-4301-02 | 0338-9560-01
4 mL | 0338-4211-04 | 0338-4302-04 | 0338-9564-01
10 mL | 0338-4212-10 | 0338-4303-10 | 0338-9568-01

TISSEEL Kit contains one vial each of:

1. Sealer Protein Concentrate (Human), Vapor Heated, Solvent/Detergent Treated, Freeze-Dried, Sterile
2. Fibrinolysis Inhibitor Solution, Aprotinin (Synthetic) Liquid, Sterile
3. Thrombin (Human), Vapor Heated, Solvent/Detergent Treated, Freeze-Dried, Sterile
4. Calcium Chloride Solution, Liquid, Sterile
5. With and without DUPLOJECT Fibrin Sealant Preparation and Application System

TISSEEL Pre-Filled Dual-Chambered Syringe contains:

1. Sealer Protein Solution, Vapor Heated, Solvent/Detergent Treated, Frozen Solution, Sterile
2. Thrombin Solution, Vapor Heated, Solvent/Detergent Treated, Frozen Solution, Sterile
3. Sterile accessory devices (DUPLOJECT COMBI)

Storage and Handling
TISSEEL Kit (Freeze-Dried)
Store at 2-25°C. Avoid freezing. Do not freeze or refrigerate reconstituted solutions.

TISSEEL Pre-filled Syringe (Frozen)
Store at ≤ -20°C. Do not refrigerate or re-freeze after thawing. Once removed from the freezer, TISSEEL must be used within 48 hours. Prior to application, TISSEEL must be warmed to 33 - 37˚C.
Once the pouches are opened or warmed to 33-37°C, they must be used within 4 hours.
Do not use after the expiration date. Discard if packaging of any components is damaged.

17 PATIENT COUNSELING INFORMATION

Discuss following with the patient and/or caregivers.

- Hypersensitivity Reactions: Inform the patient and/or caregivers that hypersensitivity reactions may occur with TISSEEL and advise to seek immediate medical evaluation if any signs and symptoms of hypersensitivity occur. These may include bradycardia, tachycardia, hypotension, flushing, bronchospasm, wheezing, dyspnea, nausea, urticaria, angioedema, pruritus, erythema and paresthesia [see Warnings and Precautions (5.1)].
- Transmission of Infectious agents: Inform the patient and/or caregivers that TISSEEL is made from human plasma and may carry a risk of transmitting infectious agents (e.g., viruses, the vCJD agent and, theoretically, the CJD agent). Instruct patients to report any symptoms that concern them and might be caused by infections [see Warnings and Precautions (5.5)].
  Instruct patients to consult their physician if symptoms of B19 virus infection appear (fever, drowsiness, chills and runny nose) followed about two weeks later by a rash and joint pain (see Use in Specific Populations (8.1)).

Manufactured For Baxter Healthcare Corporation
Deerfield, IL 60015 USA
US License No. 140

Baxter, Artiss, Duploject, Duploject Combi, Duplospray, Easyspray, Fibrinotherm and Tisseel are trademarks of Baxter International Inc. or its subsidiaries.

PACKAGE/LABEL PRINCIPAL DISPLAY PANEL

Tissel Lyo 2 mL Vial Carton Label

NDC 0338-4210-02

Fibrin Sealant
TISSEEL 2 mL
Vapor Heated, Solvent/Detergent Treated, Kit

GTIN (01)
LOT (10)
EXPIRY (17)
SERIAL (21)

Baxter Logo

NDC 0338-4210-02

Barcode

Fibrin Sealant
TISSEEL 2 mL
Vapor Heated, Solvent/Detergent Treated, Kit

Contents:

Sealer Protein Concentrate (Human), Vapor Heated,
Solvent/Detergent Treated, freeze dried, sterile, for
1 mL of Sealer Protein Solution 86.5 mg/mL

Fibrinolysis Inhibitor Solution (Synthetic), sterile,
3000 KIU of Aprotinin /mL

Thrombin (Human), Vapor Heated, Solvent/Detergent
Treated, freeze dried, sterile, for 1 mL of Thrombin
Solution 500 units/mL

Calcium Chloride Solution, sterile, 40 μmol /mL

The risks and benefits of this product should be discussed
with the patient.
Read enclosed directions for reconstitution and application
before use.
Use within four hours of reconstitution.

NOT FOR INJECTION. For single use only.

Not made with natural rubber latex

Rx only

Manufactured for Baxter Healthcare Corporation
Deerfield, IL 60015 USA

U.S. License No. 140

Made in Austria

U.S. Pat. No.: 5,962,405

Baxter and Tisseel are trademarks of Baxter International Inc.

0752668

Fibrin Sealant
TISSEEL 2 mL
Vapor Heated, Solvent/
Detergent Treated, Kit

2 mL

Store at 2°C to 25°C (36°F to 77°F).
Avoid freezing.

Tisseel Lyo 2mL Sleeve Carton Label

Baxter Logo

NDC 0338-4301-02

Fibrin Sealant
TISSEEL 2 mL
Vapor Heated, Solvent/Detergent Treated, Kit

Manufactured for Baxter Healthcare Corporation
Deerfield, IL 60015 USA

U.S. License No. 140

Made in Austria

Reorder Number: 1504514

Baxter, Duploject and Tisseel are trademarks of Baxter International Inc.

U.S. Pat. No.: 5,962,405

Baxter Logo

NDC 0338-4301-02

Fibrin Sealant
TISSEEL 2 mL
Vapor Heated, Solvent/Detergent Treated, Kit

TOPICAL USE ONLY
DO NOT INJECT

Baxter Logo

NDC 0338-4301-02

Barcode

Fibrin Sealant
TISSEEL 2 mL
Vapor Heated, Solvent/Detergent Treated, Kit

Contents:

Sealer Protein Concentrate (Human), Vapor Heated,
Solvent/Detergent Treated, freeze dried, sterile, for
1 mL of Sealer Protein Solution 86.5 mg/mL

Fibrinolysis Inhibitor Solution (Synthetic), sterile,
3000 KIU of Aprotinin /mL

Thrombin (Human), Vapor Heated, Solvent /Detergent
Treated, freeze dried, sterile, for 1 mL of Thrombin Solution
500 units/mL

Calcium Chloride Solution, sterile, 40 μmol /mL

The risks and benefits of this product should be discussed
with the patient. Read enclosed directions for
reconstitution and application before use. Use within four
hours of reconstitution.

NOT FOR INJECTION. For single use only.

Not made with natural rubber latex
Rx only

Also includes: DUPLOJECT Fibrin Sealant Preparation and Application System 2 mL / 4 mL

0752670

Barcode

Barcode
N3 0338-4301-02 3

Tisseel Lyo 2 mL - 4 mL DUPLOJET Label

Baxter Logo

DUPLOJET 2 mL / 4 mL

Fibrin Sealant Preparation and
Application System

Baxter Logo

DUPLOJET 2 mL / 4 mL

Fibrin Sealant Preparation and
Application System

BAXTER, DUPLOJET and TISSEEL are trademarks of
Baxter International Inc., registered in the U.S. Patent and
Trademark office.

Manufactured for:
Baxter Healthcare Corporation
One Baxter Parkway
Deerfield, IL 60015 USA

DUPLOJET 2 mL / 4 mL
Fibrin Sealant Preparation and
Application System

For Fibrin Sealant
2 mL or 4 mL Kit

2 mL
4 mL

Indications for Use:
For the preparation and application of TISSEEL
[Fibrin Sealant] 2 mL / 4 mL Kit.

STERILE – SINGLE PATIENT USE ONLY – DO NOT RESTERILIZE

Use separate devices for reconstruction of Sealer Protein Concentrate
and Thrombin.

Rx only

Made in Belgium

Barcode

BE8001137

BE-80-01-137

DUPLOJET 2 mL / 4 mL
Fibrin Sealant Preparation and
Application System

For Fibrin Sealant
2 mL or 4 mL Kit

2 mL
4 mL

DUPLOJET IFU Label

Baxter Logo
BE_30-02-680

DUPLOJECT
Fibrin Sealant Preparation and Application System

Indications for Use:

For the preparation and application of TISSEEL [Fibrin Sealant] kit.

Note: See TISSEEL Fibrin Sealant package insert for additional preparation and
application instructions.

1.0 Reconstitution Instructions for the Circulating Nurse (Using the FIBRINO-
THERM Heating and Stirring Device)

1.1 Turn on the warming unit of the FIBRINOTHERM device (amber switch).

1.2 Open TISSEEL [Fibrin Sealant] kit and place all vials into the appropriately sized
heating wells of the FIBRINOTHERM device.

1.3 Place the Sealer Protein vial into the large magnetic stirring well fitted with
the appropriately sized adapter ring (if necessary). Do not activate the stirring
mechanism at this time. The indicator light will remain lit until a temperature of
37°C (98.6°F) is reached. Allow several minutes for proper warming.

1.4 Open Pack A of the DUPLOJECT Preparation and Application System and
assemble the blue-scaled and black-scaled syringes with the needles provided.

1.5 Remove the flip-off caps from the blue-capped Sealer Protein Concentrate
and Fibrinolysis Inhibitor Solution vials and wipe with a non-iodine based dis-
infectant.

1.6 Using the blue-scaled syringe, withdraw the Fibrinolysis Inhibitor Solution from
the vial, tilting the vial slightly to facilitate removal of all solution. Inject the
Fibrinolysis Inhibitor Solution into the Sealer Protein Concentrate vial. Gently
swirl the vial to ensure that the freeze-dried material is fully soaked. Note: Do not
invert or inject air into vials.

1.7 Place the Sealer Protein Concentrate vial in the stirring well and activate the
stirring mechanism of the FIBRINOTHERM device (green switch). Reconstitution
is complete when no undissolved particles are visible. If Sealer Protein is not fully
dissolved after 20 minutes, discard and prepare a fresh kit. Continue with steps 8
through 11.

1.8 Remove the flip-off caps from the black-capped Thrombin and Calcium Chloride
Solution vials and wipe with a non-iodine based disinfectant.

1.9 Using the black-scaled syringe, withdraw the Calcium Chloride Solution from the
vial, tilting the vial slightly to facilitate removal of all solution. Inject the Calcium
Chloride Solution into the Thrombin vial. Note: Do not invert or inject air into vials.

1.10 Swirl contents of the Thrombin vial briefly and return it to an appropriately sized
heating well in the FIBRINOTHERM device.

1.11 Leave the Sealer Protein and Thrombin vials in the FIBRINOTHERM device until
the solutions are ready to be passed into the sterile field.

2.0 Preparation Instructions for the Scrub Nurse

2.1 Open Pack B of the DUPLOJECT Preparation and Application System into the
sterile field.

2.2 Open Packs 1, 2, and 3.

2.3 Assemble the blue-scaled and black-scaled syringes with the needles provided.
Note: For 5 mL DUPLOJECT systems, attach the larger needle to the blue-scaled
syringe.

2.4 While the Circulating Nurse holds the vial slightly tilted, insert needle into
vial (bevel side down) and withdraw all of the Sealer Protein Solution into the
blue-scaled syringe using slow, constant aspiration. Discard needle in sharps
container.

2.5 While the Circulating Nurse holds the vial slightly tilted, insert needle into vial
(bevel side down) and withdraw all of the Thrombin Solution into the black-scaled
syringe using slow, constant aspiration. Discard needle in sharps container.

2.6 Remove any air bubbles from the syringes and ensure both syringes contain the
same volume.

2.7 Snap the filled syringes into the two-syringe clip with the flanges in an up/down
position, as illustrated below.

2.8 Attach the joining piece to the syringe nozzles, ensuring that both are firmly
seated. Secure the joining piece by fastening the retaining strap to the double
syringe clip. Note: Align the syringe nozzles toward the middle for proper
attachment.

2.9 Fit one of the application needles onto the joining piece. A second application
needle is provided in Pack 3 as a spare.

2.10 DUPLOJECT Applicator is ready for use.

2.11 If application of TISSEEL [Fibrin Sealant] is interrupted, replace the needle
immediately before application is resumed. Note: If the apertures of the joining
piece become clogged, Pack 4 contains one spare joining piece and two
additional application needles.

Rx Only
DO NOT REUSE OR RESTERILIZE.
NOT MADE WITH NATURAL RUBBER LATEX.

STERILE AND NON-PYROGENIC IN UNOPENED AND UNDAMAGED PACKAGE.

DISPOSE OF CONTAMINATED AND SHARP COMPONENTS PROPERLY.

Baxter, Duploject, Fibrinotherm and Tisseel are registered trademarks of Baxter International Inc.

Manufactured for:
Baxter Healthcare Corporation
One Baxter Parkway
Deerfield, IL 60015 USA
1-888-229-0001

Made in Belgium

Rev. Date: 2017-05-17

2 mL PRIMA Pouch Label

Fibrin Sealant
TISSEEL 2 mL

NDC 0338-9560-01

Vapor Heated, Solvent/Detergent Treated, Frozen

Baxter Logo

Temperature sensitive – Do NOT expose above 37°C (99°F).

TOPICAL USE ONLY DO NOT INJECT

Read directions for thawing and application before use.
Store at –20°C (–4°F) or colder. Unopened pouches
may be stored for up to 48 hours at room temperature
(15 – 25°C).

Do not refrigerate or re-freeze.

Rx Only

Contents:
Pre-filled syringe containing:
– Sealer Protein Solution (1): 1 mL, sterile
– Fibrinogen (Human), 86.5 mg/mL
– Fibrinolysis Inhibitor (Aprotinin,
Synthetic), 3000 KIU/mL

– Thrombin Solution (2): 1 mL, sterile
– Thrombin (Human), 500 units/mL
– Calcium Chloride, 40 ìmol/mL

Manufactured for
Baxter Healthcare
Corporation
Deerfield, IL 60015 USA
U.S. License No. 140
0752652

Barcode

Lot No.:
Exp. Date:

2 mL PRIMA Carton Label

0752653

Fibrin Sealant
TISSEEL
Vapor Heated, Solvent/
Detergent Treated, Frozen
TOPICAL USE ONLY

NDC 0338-9560-01
Barcode

Barcode
3 03389 56001 2

2 mL

Fibrin Sealant
TISSEEL
Vapor Heated, Solvent/Detergent Treated, Frozen
with Pre-filled PRIMA Syringe

TOPICAL USE ONLY

Contents:
Pre-filled syringe containing:
Sealer Protein Solution: 1 mL, sterile

– Fibrinogen (Human), 86.5 mg/mL
– Fibrinolysis Inhibitor (Aprotinin, Synthetic),
3000 KIU/mL

Thrombin Solution: 1 mL, sterile
– Thrombin (Human), 500 units/mL
– Calcium Chloride, 40 μmol /mL

The risks and benefits of this product should
be discussed with the patient.

Rx Only

DO NOT INJECT

Store at –20°C (–4°F) or colder.

Read enclosed directions for thawing and
application before use.

Unopened pouches may be stored for up to
48 hours at room temperature (15 – 25°C).

Do not refrigerate or re-freeze.

Not made with natural rubber latex
For Single Patient Use Only.

NDC 0338-9560-01

Fibrin Sealant
TISSEEL
Vapor Heated, Solvent/Detergent Treated, Frozen
TOPICAL USE ONLY
2 mL

Fibrin Sealant
TISSEEL
Vapor Heated, Solvent/
Detergent Treated, Frozen
TOPICAL USE ONLY
2 mL

Fibrin Sealant
TISSEEL
Vapor Heated, Solvent/
Detergent Treated, Frozen
TOPICAL USE ONLY
2 mL

Fibrin Sealant
TISSEEL
Vapor Heated, Solvent/Detergent Treated, Frozen
with Pre-filled PRIMA Syringe

TOPICAL USE ONLY

DO NOT INJECT

U.S. Pat. No.: 5,962,405

Manufactured for
Baxter Healthcare Corporation

Deerfield IL, 60015 USA

1-888-229-0001

U.S. License No. 140

Made in Austria

Reorder Number: 1506078

Baxter and Tisseel are trademarks of
Baxter International Inc.

2 mL

GTIN (01) 00303389560012

EXPIRY (17)
LOT (10)
SERIAL (21)

Baxter Logo

Fibrin Sealant
TISSEEL
Vapor Heated, Solvent/
Detergent Treated, Frozen
TOPICAL USE ONLY
2 mL

4 mL PRIMA Pouch Label

Fibrin Sealant
TISSEEL 4 mL

NDC 0338-9564-01
Barcode

Vapor Heated, Solvent/Detergent Treated, Frozen

Baxter Logo

Temperature sensitive – Do NOT expose above 37°C (99°F).

TOPICAL USE ONLY DO NOT INJECT

Read directions for thawing and application before use.
Store at –20°C (–4°F) or colder. Unopened pouches
may be stored for up to 48 hours at room temperature
(15 – 25°C).

Do not refrigerate or re-freeze.

Rx Only

Contents:
Pre-filled syringe containing:
– Sealer Protein Solution (1): 2 mL, sterile
– Fibrinogen (Human), 86.5 mg/mL
– Fibrinolysis Inhibitor (Aprotinin,
Synthetic), 3000 KIU/mL

– Thrombin Solution (2): 2 mL, sterile
– Thrombin (Human), 500 units/mL
– Calcium Chloride, 40 µmol/mL

Barcode

Manufactured for
Baxter Healthcare
Corporation
Deerfield, IL 60015 USA
U.S. License No. 140

0752656

Barcode

Lot No.:
Exp. Date:

4 mL PRIMA Carton Label

0752657

Barcode
3 03389 56401 0

Fibrin Sealant
TISSEEL
Vapor Heated, Solvent/Detergent Treated, Frozen
TOPICAL USE ONLY
with Pre-filled PRIMA Syringe

NDC 0338-9564-01

TOPICAL USE ONLY

Contents:
Pre-filled syringe containing:
Sealer Protein Solution: 2 mL, sterile
– Fibrinogen (Human), 86.5 mg/mL
– Fibrinolysis Inhibitor (Aprotinin, Synthetic),
3000 KIU/mL

Thrombin Solution: 2 mL, sterile
– Thrombin (Human), 500 units/mL
– Calcium Chloride, 40 μmol /mL

The risks and benefits of this product should
be discussed with the patient.

Rx Only

DO NOT INJECT

Store at –20°C (–4°F) or colder.

Read enclosed directions for thawing and
application before use.

Unopened pouches may be stored for up to
48 hours at room temperature (15 – 25°C).

Do not refrigerate or re-freeze.

Not made with natural rubber latex
For Single Patient Use Only.

Fibrin Sealant
TISSEEL
Vapor Heated, Solvent/
Detergent Treated, Frozen
TOPICAL USE ONLY
4 mL

Fibrin Sealant
TISSEEL
Vapor Heated, Solvent/
Detergent Treated, Frozen
TOPICAL USE ONLY
4 mL

Fibrin Sealant
TISSEEL
Vapor Heated, Solvent/
Detergent Treated, Frozen
TOPICAL USE ONLY
4 mL

Fibrin Sealant
TISSEEL
Vapor Heated, Solvent/Detergent Treated, Frozen
with Pre-filled PRIMA Syringe

TOPICAL USE ONLY

DO NOT INJECT

U.S. Pat. No.: 5,962,405

Manufactured for
Baxter Healthcare Corporation

Deerfield IL, 60015 USA

1-888-229-0001

U.S. License No. 140

Made in Austria

Reorder Number: 1506079

Baxter and Tisseel are trademarks of
Baxter International Inc.

4 mL

Baxter Logo

GTIN (01) 00303389564010
LOT (10)
EXPIRY (17)
SERIAL (21)

10 mL PRIMA Pouch Label

Fibrin Sealant
TISSEEL 10 mL

NDC 0338-9568-01

Vapor Heated, Solvent/Detergent Treated, Frozen

Baxter Logo

Temperature sensitive – Do NOT expose above 37°C (99°F).

TOPICAL USE ONLY DO NOT INJECT

Read directions for thawing and application before use.

Store at –20°C (–4°F) or colder. Unopened pouches
may be stored for up to 48 hours at room temperature
(15 – 25°C).

Do not refrigerate or re-freeze.

Rx Only

Contents:

Pre-filled syringe containing:
– Sealer Protein Solution (1): 5 mL, sterile
– Fibrinogen (Human), 86.5 mg/mL
– Fibrinolysis Inhibitor (Aprotinin,
Synthetic), 3000 KIU/mL

– Thrombin Solution (2): 5 mL, sterile
– Thrombin (Human), 500 units/mL
– Calcium Chloride, 40 ìmol/mL

Manufactured for
Baxter Healthcare
Corporation
Deerfield, IL 60015 USA
U.S. License No. 140

0752660

Barcode

Barcode

Lot No.:
Exp. Date:

10mL PRIMA Carton Label

0752661

Barcode
3 03389 56801 8

Fibrin Sealant
TISSEEL
Vapor Heated, Solvent/
Detergent Treated, Frozen
TOPICAL USE ONLY

NDC 0338-9568-01
Barcode

10 mL

Fibrin Sealant
TISSEEL
Vapor Heated, Solvent/
Detergent Treated, Frozen
TOPICAL USE ONLY

10 mL

Fibrin Sealant
TISSEEL
Vapor Heated, Solvent/Detergent Treated, Frozen
with Pre-filled PRIMA Syringe

TOPICAL USE ONLY

Contents:
Pre-filled syringe containing:
Sealer Protein Solution: 5 mL, sterile
– Fibrinogen (Human), 86.5 mg/mL
– Fibrinolysis Inhibitor (Aprotinin, Synthetic),
3000 KIU/mL

Thrombin Solution: 5 mL, sterile
– Thrombin (Human), 500 units/mL
– Calcium Chloride, 40 μmol /mL

The risks and benefits of this product should
be discussed with the patient.

Rx Only

DO NOT INJECT

Store at –20°C (–4°F) or colder.

Read enclosed directions for thawing and
application before use.

Unopened pouches may be stored for up to
48 hours at room temperature (15 – 25°C).

Do not refrigerate or re-freeze.

Not made with natural rubber latex

For Single Patient Use Only

Fibrin Sealant
TISSEEL
Vapor Heated, Solvent/
Detergent Treated, Frozen
TOPICAL USE ONLY

10 mL

Fibrin Sealant
TISSEEL
Vapor Heated, Solvent/
Detergent Treated, Frozen
TOPICAL USE ONLY
10 mL

Barcode

Fibrin Sealant
TISSEEL
Vapor Heated, Solvent/Detergent Treated, Frozen
with Pre-filled PRIMA Syringe

TOPICAL USE ONLY

DO NOT INJECT

U.S. Pat. No.: 5,962,405

Manufactured for
Baxter Healthcare Corporation

Deerfield IL, 60015 USA

1-888-229-0001

U.S. License No. 140

Made in Austria

Reorder Number: 1506080

Baxter and Tisseel are trademarks of
Baxter International Inc.

10 mL

Baxter Logo

GTIN (01) 00303389568018
EXPIRY (17)
LOT (10)
SERIAL (21)

Lyo 4mL Vial Carton Label

GTIN (01)
LOT (10)
EXPIRY (17)

SERIAL (21)

NDC 0338-4211-04

Fibrin Sealant
TISSEEL 4 mL
Vapor Heated, Solvent/Detergent Treated, Kit

Baxter logo

NDC 0338-4211-04
barcode

Fibrin Sealant
TISSEEL 4 mL
Vapor Heated, Solvent/Detergent Treated, Kit

Contents:
Sealer Protein Concentrate (Human), Vapor Heated,
Solvent /Detergent Treated, freeze dried, sterile, for
2 mL of Sealer Protein Solution
Fibrinolysis Inhibitor Solution (Synthetic), sterile,
3000 KIU of Aprotinin /mL
Thrombin (Human), Vapor Heated, Solvent /Detergent
Treated, freeze dried, sterile, for 2 mL of Thrombin
Solution 500 units/mL
Calcium Chloride Solution, sterile, 40 μmol /mL

The risks and benefits of this product should be discussed
with the patient.
Read enclosed directions for reconstitution and application
before use.
Use within four hours of reconstitution.
NOT FOR INJECTION. For single use only.
Not made with natural rubber latex
Rx only

Manufactured for Baxter Healthcare Corporation
Deerfield, IL 60015 USA

U.S. License No. 140

Made in Austria

Baxter and Tisseel are trademarks of Baxter International Inc.

U.S. Pat. No.: 5,962,405

Barcode
0752678

Fibrin Sealant
TISSEEL 4 mL
Vapor Heated, Solvent/
Detergent Treated, Kit

4 mL

Store at 2°C to 25°C (36°F to 77°F).
Avoid freezing.

Lyo 10mL Vial Carton Label

GTIN (01)
LOT (10)
EXPIRY (17)

SERIAL (21)

NDC 0338-4212-10

Fibrin Sealant
TISSEEL 10 mL
Vapor Heated, Solvent/Detergent Treated, Kit

Baxter Logo

NDC 0338-4212-10
barcode

Fibrin Sealant
TISSEEL 10 mL
Vapor Heated, Solvent/Detergent Treated, Kit

Contents:
Sealer Protein Concentrate (Human), Vapor Heated,
Solvent /Detergent Treated, freeze dried, sterile, for
5 mL of Sealer Protein Solution 86.5 mg/mL

Fibrinolysis Inhibitor Solution (Synthetic), sterile,
3000 KIU of Aprotinin /mL

Thrombin (Human), Vapor Heated, Solvent /Detergent
Treated, freeze dried, sterile, for 5 mL of Thrombin
Solution 500 units/mL

Calcium Chloride Solution, sterile, 40 µmol /mL

The risks and benefits of this product should be discussed
with the patient.
Read enclosed directions for reconstitution and application
before use.
Use within four hours of reconstitution.

NOT FOR INJECTION. For single use only.

Not made with natural rubber latex

Rx only

Manufactured for Baxter Healthcare Corporation
Deerfield, IL 60015 USA

U.S. License No. 140

Made in Austria

Baxter and Tisseel are trademarks of Baxter International Inc.

U.S. Pat. No.: 5,962,405

Barcode

0752688

Fibrin Sealant
TISSEEL 10 mL
Vapor Heated, Solvent/
Detergent Treated, Kit

10 mL

Store at 2°C to 25°C (36°F to 77°F).
Avoid freezing.

Lyo 4mL Sleeve Carton Label

Baxter Logo

NDC 0338-4302-04

Fibrin Sealant
TISSEEL 4 mL
Vapor Heated, Solvent/Detergent Treated, Kit

Manufactured for Baxter Healthcare Corporation
Deerfield, IL 60015 USA

U.S. License No. 140

Made in Austria

Reorder Number: 1504515

Baxter, Duploject and Tisseel are trademarks of Baxter International Inc.

U.S. Pat. No.: 5,962,405

Baxter Logo

NDC 0338-4302-04

Fibrin Sealant
TISSEEL 4 mL
Vapor Heated, Solvent/Detergent Treated, Kit

TOPICAL USE ONLY
DO NOT INJECT

Baxter Logo

NDC 0338-4302-04
barcode

Fibrin Sealant
TISSEEL 4 mL
Vapor Heated, Solvent/Detergent Treated, Kit

Contents:
Sealer Protein Concentrate (Human), Vapor Heated,
Solvent /Detergent Treated, freeze dried, sterile, for
2 mL of Sealer Protein Solution 86.5 mg/mL

Fibrinolysis Inhibitor Solution (Synthetic), sterile,
3000 KIU of Aprotinin /mL

Thrombin (Human), Vapor Heated, Solvent /Detergent
Treated, freeze dried, sterile, for 2 mL of Thrombin Solution
500 units/mL

Calcium Chloride Solution, sterile, 40 μmol /mL

The risks and benefits of this product should be discussed
with the patient. Read enclosed directions for
reconstitution and application before use. Use within four
hours of reconstitution.

NOT FOR INJECTION. For single use only.

Not made with natural rubber latex

Rx only

Also includes: DUPLOJECT Fibrin Sealant Preparation and Application System 2 mL / 4 mL

0752680

Barcode

Barcode
N3 0338-4302-04 4

Lyo 10mL Sleeve Carton Label

Baxter Logo

NDC 0338-4303-10

Fibrin Sealant
TISSEEL 10 mL
Vapor Heated, Solvent/Detergent Treated, Kit

Manufactured for Baxter Healthcare Corporation
Deerfield, IL 60015 USA

U.S. License No. 140

Made in Austria

Reorder Number: 1504516

Baxter, Duploject and Tisseel are trademarks of Baxter International Inc.

U.S. Pat. No.: 5,962,405

Baxter Logo

NDC 0338-4303-10

Fibrin Sealant
TISSEEL 10 mL
Vapor Heated, Solvent/Detergent Treated, Kit

TOPICAL USE ONLY
DO NOT INJECT

Baxter Logo

NDC 0338-4303-10

Barcode

Fibrin Sealant
TISSEEL 10 mL
Vapor Heated, Solvent/Detergent Treated, Kit

Contents:
Sealer Protein Concentrate (Human), Vapor Heated,
Solvent /Detergent Treated, freeze dried, sterile, for
5 mL of Sealer Protein Solution 86.5 mg/mL

Fibrinolysis Inhibitor Solution (Synthetic), sterile,
3000 KIU of Aprotinin /mL

Thrombin (Human), Vapor Heated, Solvent /Detergent
Treated, freeze dried, sterile, for 5 mL of Thrombin Solution
500 units/mL

Calcium Chloride Solution, sterile, 40 μmol /mL

The risks and benefits of this product should be discussed
with the patient. Read enclosed directions for
reconstitution and application before use. Use within four
hours of reconstitution.
NOT FOR INJECTION. For single use only.
Not made with natural rubber latex
Rx only

Also includes: DUPLOJECT Fibrin Sealant Preparation and Application System 10 mL

0752690

Barcode

Barcode
N3 0338-4303-10 2

Duploject Combi Label

Baxter Logo

DuploJect Combi
Indication for Use:
For the application of TISSEEL Fibrin Sealant.

REF
Batch code
Use-by date

For single use only. Not made with natural rubber latex.
Do not reuse or resterilize. Sterilized using ethylene oxide.
Sterile and non-pyrogenic in unopened and undamaged package. Rx Only.

Manufactured for:
Baxter Healthcare Corporation
One Baxter Parkway
Deerfield, IL 60015 USA
1-888-229-0001

Made in Belgium

BE-90-01-044